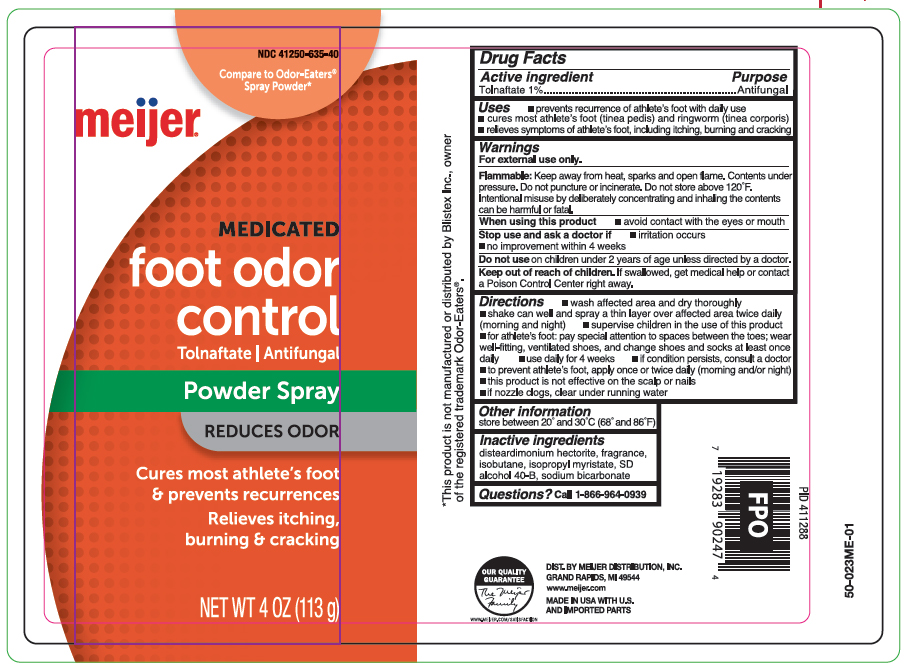 DRUG LABEL: Tolnaftate
NDC: 41250-635 | Form: AEROSOL, SPRAY
Manufacturer: Meijer Distribution Inc
Category: otc | Type: HUMAN OTC DRUG LABEL
Date: 20260120

ACTIVE INGREDIENTS: TOLNAFTATE 1.3 g/113 g
INACTIVE INGREDIENTS: DISTEARDIMONIUM HECTORITE; ISOBUTANE; ALCOHOL; SODIUM BICARBONATE

Foot Odor Control Powder Spray

Active ingredient

Tolnaftate 1%

Purpose

Antifungal

Uses

- prevents recurrence of athlete's foot with daily use
- cures mose athlete's foot (tinea pedis) and ringworm (tinea corporis)
- relieves sypmtoms of athlete's foot, including itching, burning and cracking

Warnings

For external use only.

Flammable:

Keep away from heat, sparks and open flame. Contents under pressure. Do not puncture or incinerate. Do not store above 120°F. Intentional misuse by deliberately concentrating and inhaling the contents cans be harmful or fatal.

When using this product

- avoid contact with the eyes or mouth

Stop use and ask a doctor if

- irritation occurs
- no improvement within 4 weeks

Do not use

on children under 2 years of age unless directed by a doctor.

Keep out of reach of children.

If swallowed, get medical help or contact a Poison Control Center right away.

Directions

- wash affected area and dry thoroughly
- shake can well and spray a thin layer over affected area twice daily (morning and night)
- supervise children in the use of this product
- for athlete's foot: pay special attention to spaces between the toes; wear well-fitting, ventilated shoes, and change shoes and socks at least once daily
- use daily for 4 weeks
- if conditions persists, consult a doctor
- to prevent athlete's foot, apply once or twice daily (morning and/or night)
- this product is not effective on the scalp or nails
- if nozzle clogs, clear nozzle under running water

Other information

store between 20º and 30ºC (68º and 86ºF)

Inactive ingredients

disteardimonium hectorite, fragrance, isobutane, isopropyl myristate, SD alcohol 40-B, sodium bicarbonate

Questions?

call 1-866-964-0939

Principal Display Panel

meijer

MEDICATED

foot odor control

Tolnaftate | Antifungal

Powder Spray

REDUCES ODOR

Cures most athlete's foot

& prevents recurrences

Relieves itching,

burning & cracking

NET WT 4 OZ (113g)